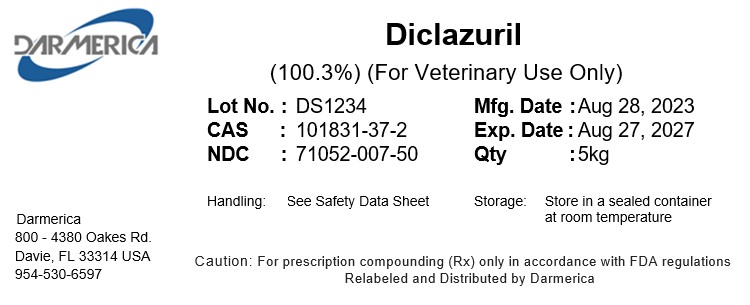 DRUG LABEL: Diclazuril
NDC: 71052-007 | Form: POWDER
Manufacturer: DARMERICA, LLC
Category: other | Type: BULK INGREDIENT - ANIMAL DRUG
Date: 20241220

ACTIVE INGREDIENTS: DICLAZURIL 1 kg/1 kg

Diclazuril